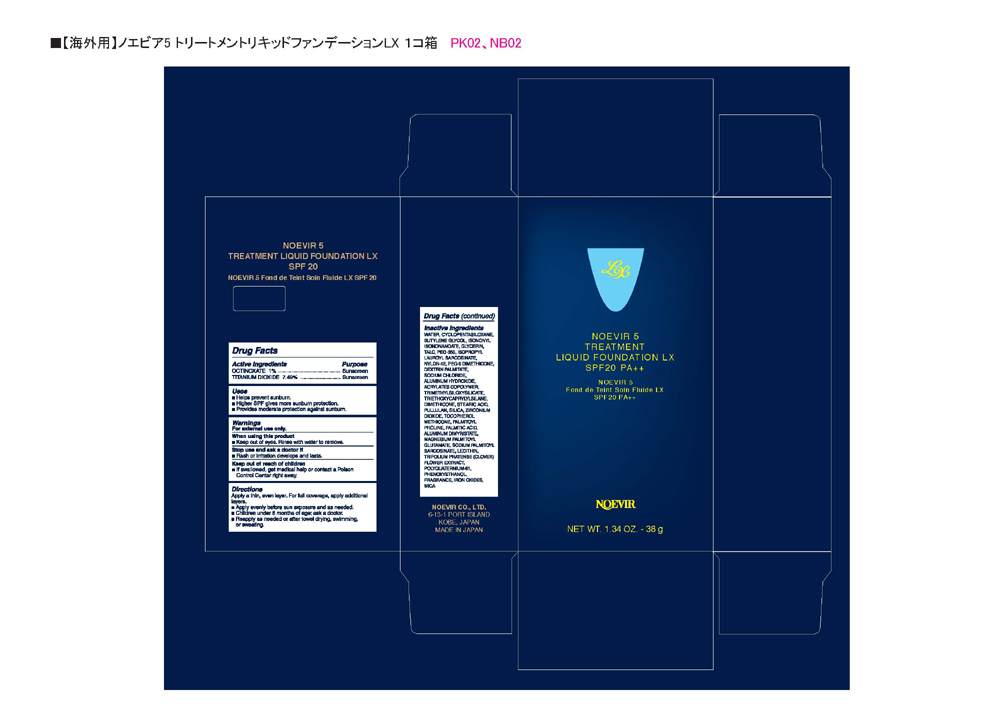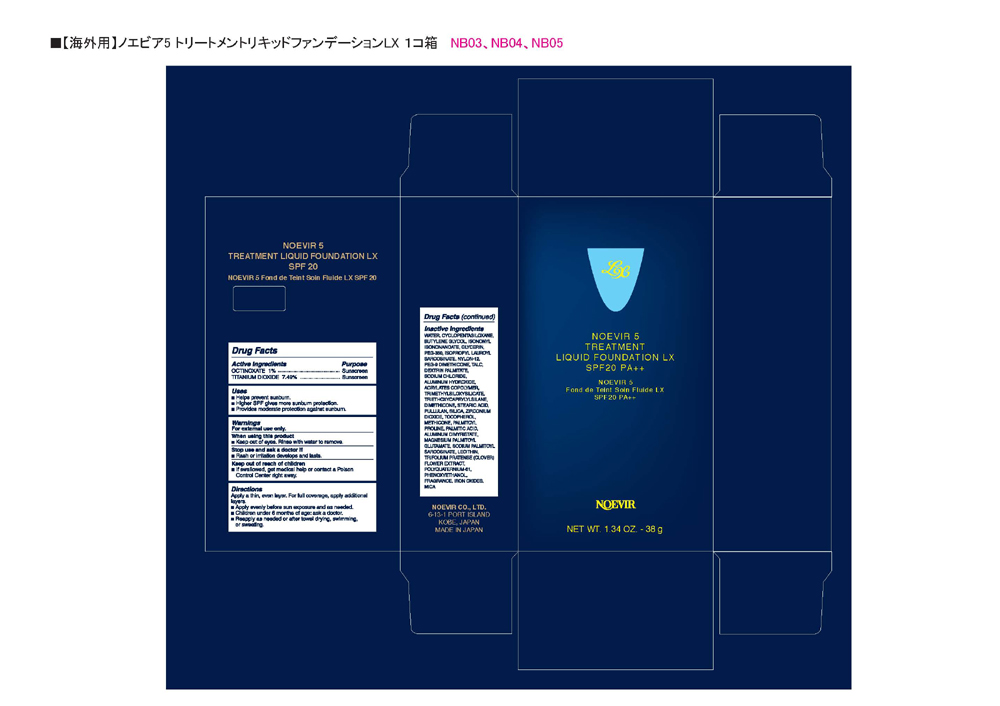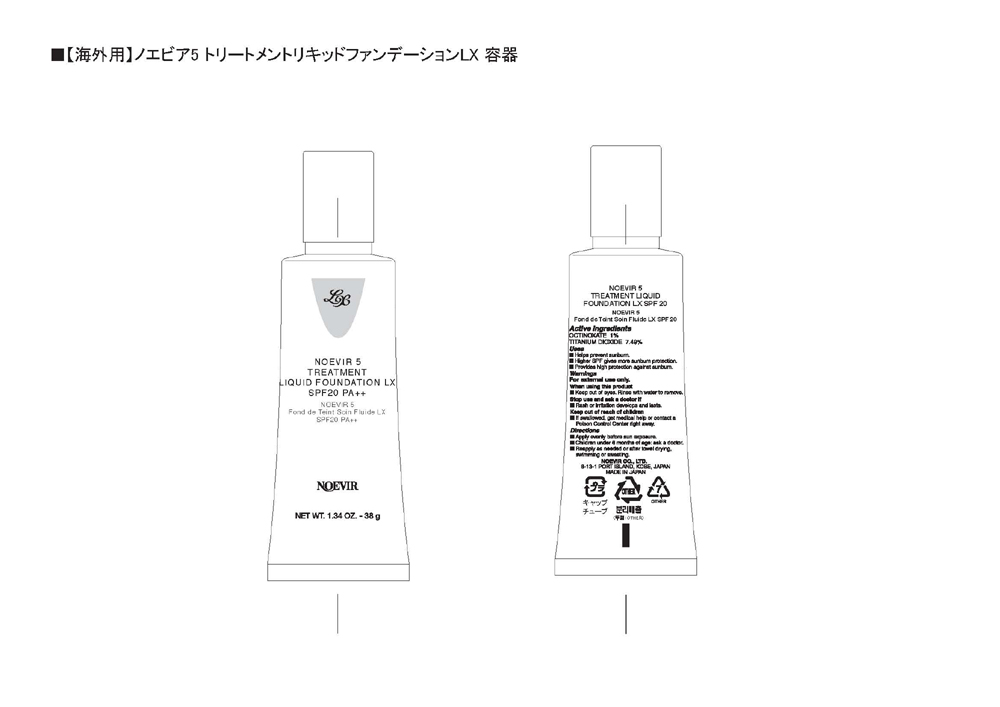 DRUG LABEL: NOEVIR 5 TREATMENT LIQUID FOUNDATION LX
NDC: 62908-013 | Form: LIQUID
Manufacturer: NOEVIR USA INC
Category: otc | Type: HUMAN OTC DRUG LABEL
Date: 20100801

ACTIVE INGREDIENTS: OCTINOXATE 1000 mg/100 g; TITANIUM DIOXIDE 7490 mg/100 g

Drug Facts

Drug Facts

Active Ingredients Purpose
OCTINOXATE 1% Sunscreen
TITANIUM DIOXIDE 7.49% Sunscreen
Uses

- Helps prevent sunburn.
- Higher SPF gives more sunburn protection.
- Provides high protection against sunburn.

Warnings
For external use only.
When using this product

- Keep out of eyes. Rinse with water to remove.

Stop use and ask a doctor if

- Rash or irritation develops and lasts.

Keep out of reach of children

- If swallowed, get medical help or contact a Poison Control Center right away.

Directions
Apply a thin, even layer. For full coverage, apply additional layers.

- Apply evenly before sun exposure.
- Children under 6 months of age ask a doctor.
- Reapply as needed or after towel drying, swimming or sweating.